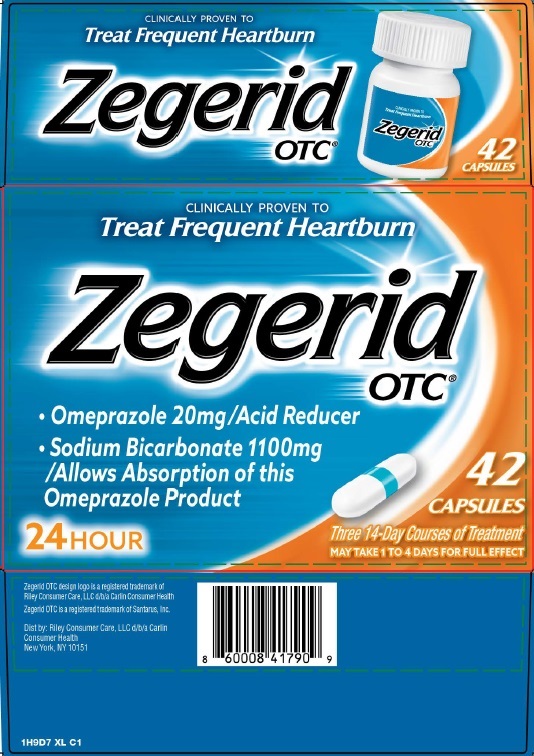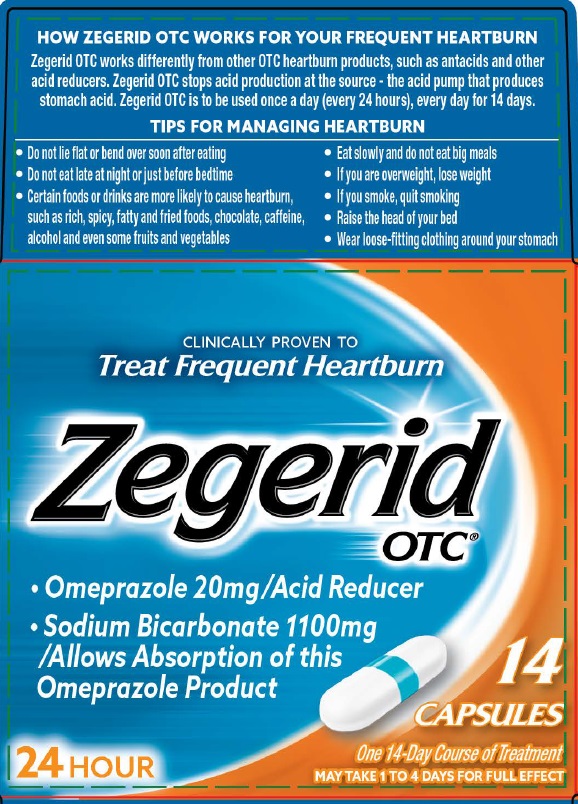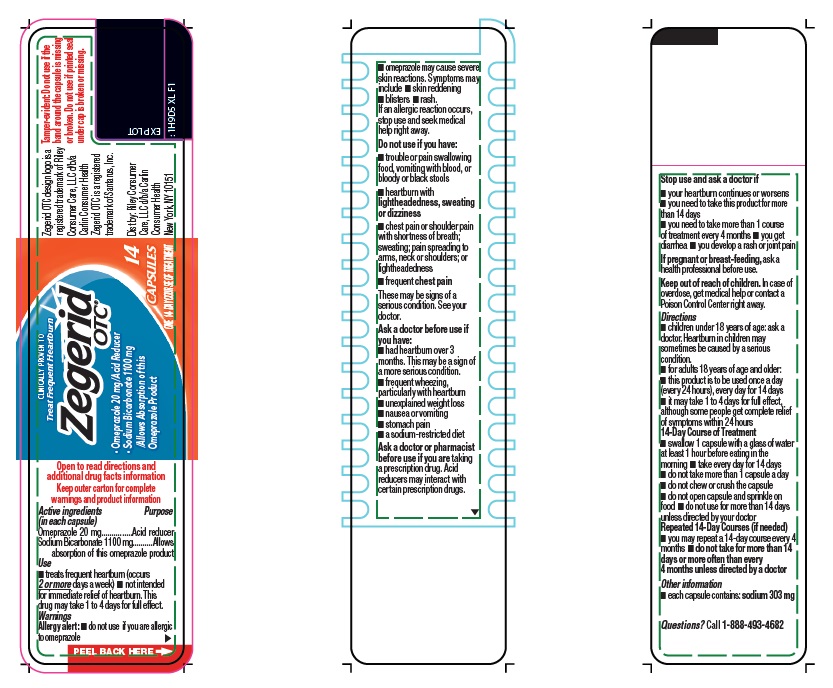 DRUG LABEL: Zegerid OTC
NDC: 82632-100 | Form: CAPSULE
Manufacturer: Riley Consumer Care LLC
Category: otc | Type: HUMAN OTC DRUG LABEL
Date: 20251224

ACTIVE INGREDIENTS: Omeprazole 20 mg/1 1; Sodium Bicarbonate 1100 mg/1 1
INACTIVE INGREDIENTS: Fd&C Blue No. 1; Fd&C Blue No. 2 Aluminum Lake; Fd&C Red No. 40; Gelatin, Unspecified; Polysorbate 80; Sodium Lauryl Sulfate; Sodium Starch Glycolate Type A; Sodium Stearyl Fumarate; Titanium Dioxide

Drug Facts

Active Ingredients (in each capsule) | Purpose
Omeprazole 20 mg | Acid reducer
Sodium Bicarbonate 1100 mg | Allows absorption of this omeprazole product

Use

- treats frequent heartburn (occurs 2 or more days a week)
- not intended for immediate relief of heartburn.
  This drug may take 1 to 4 days for full effect.

Warnings

Allergy alert:

- do not use if you are allergic to omeprazole.
- omeprazole may cause severe skin reactions
  Symptoms may include:
  - skin reddening
  - blisters
  - rash
  If an allergic reaction occurs, stop use and seek medical help right away

Do not use if you have:

- trouble or pain swallowing food, vomiting with blood, or bloody or black stools
- heartburn with lightheadedness, sweating or dizziness
- chest pain or shoulder pain with shortness of breath; sweating; pain spreading to arms, neck or shoulders; or lightheadedness
- frequent chest pain

These may be signs of a serious condition. See your doctor.

Ask a doctor before use if you have

- had heartburn over 3 months. This may be a sign of a more serious condition.
- frequent wheezing, particularly with heartburn
- unexplained weight loss
- nausea or vomiting
- stomach pain
- a sodium-restricted diet.

Ask a doctor or pharmacist before use if you are taking a prescription drug. Acid reducers may interact with certain prescription drugs.

Stop use and ask a doctor if

- your heartburn continues or worsens
- you need to take this product for more than 14 days
- you need to take more than 1 course of treatment every 4 months
- you get diarrhea
- you develop a rash or joint pain

PREGNANCY OR BREAST FEEDING

If pregnant or breast-feeding, ask a health professional before use.

Keep out of reach of children. In case of overdose, get medical help or contact a Poison Control Center right away (1-800-222-1222).

Directions

- for adults 18 years of age and older
- this product is to be used once a day (every 24 hours), every day for 14 days
- it may take 1 to 4 days for full effect, although some people get complete relief of symptoms within 24 hours

14-Day Course of Treatment

- swallow 1 capsule with a glass of water at least 1 hour before eating in the morning
- take every day for 14 days
- do not take more than 1 capsule a day
- do not chew or crush the capsule
- do not open capsule and sprinkle on food
- do not use for more than 14 days unless directed by your doctor

Repeated 14-day Courses (if needed)

- you may repeat a 14-day course every 4 months
- do not take for more than 14 days or more often than every 4 months unless directed by a doctor
- children under 18 years of age: ask a doctor
  Heartburn in children may sometimes be caused by a serious condition.

Other information

- each capsule contains: sodium 303 mg
- read the directions, warnings and accompanying label information before use
- store at 20°- 25°C (68°-77°F)
- tamper-evident: do not use if the blue band around the capsule is missing or broken. Do not use if foil inner seal imprinted with "Sealed for your protection" is missing, open or broken.
- keep product out of high heat and humidity
- protect product from moisture

Inactive Ingredients

FD&C blue no. 1, FD&C blue no. 2 aluminum lake, FD&C red no. 40, gelatin, polysorbate 80, sodium lauryl sulfate, sodium starch glycolate, sodium stearyl fumarate, titanium dioxide

Questions or comments?

Call 1-888-4-ZEG-OTC (1-888-493-4682) between: 9:00 AM and 5:00 PM Eastern Standard Time, Monday through Friday

Zegerid OTC design logo is a registered trademark of Riley Consumer Care, LLC d/b/a Carlin Consumer Health

Zegerid OTC is a registered trademark of Santarus, Inc.

Dist by: Riley Consumer Care, LLC d/b/a Carlin Consumer Health
New York, NY 10151

PACKAGE LABEL.PRINCIPAL DISPLAY PANEL

HOW ZEGERID OTC WORKS FOR YOUR FREQUENT HEARTBURN

Zegerid OTC works differently from other OTC heartburn products, such as antacids and other
acid reducers. Zegerid OTC stops acid production at the source - the acid pump that produces
stomach acid. Zegerid OTC is to be used once a day (every 24 hours), every day for 14 days.

TIIPS FOR MANAGING HEARTBURN

- Do not lie flat or bend over after eating
- Do not eat late at night or just before bedtime
- Certain foods or drinks are more likely to cause heartburn,
  such as rich, spicy, fatty and fried foods, chocolate, caffeine,
  alcohol and even some fruits and vegetables

- Eat slowly and do not eat big meals
- If you are overweight, lose weight
- If you smoke, quit smoking
- Raise the head of your bed
- Wear loose-fitting clothing around your stomach

CLINICALLY PROVEN TO
Treat Frequent Heartburn
Zegerid
OTC®

- Omperazole 20mg / Acid Reducer
- Sodium Bicarbonate 1100mg
  /Allows Absorption of this
  Omperazole Product

14 CAPSULES
One 14-Day Course of Treatment
MAY TAKE 1 TO 14 DAYS FOR FULL EFFECT
24 HOUR
1H9D5 XL C1